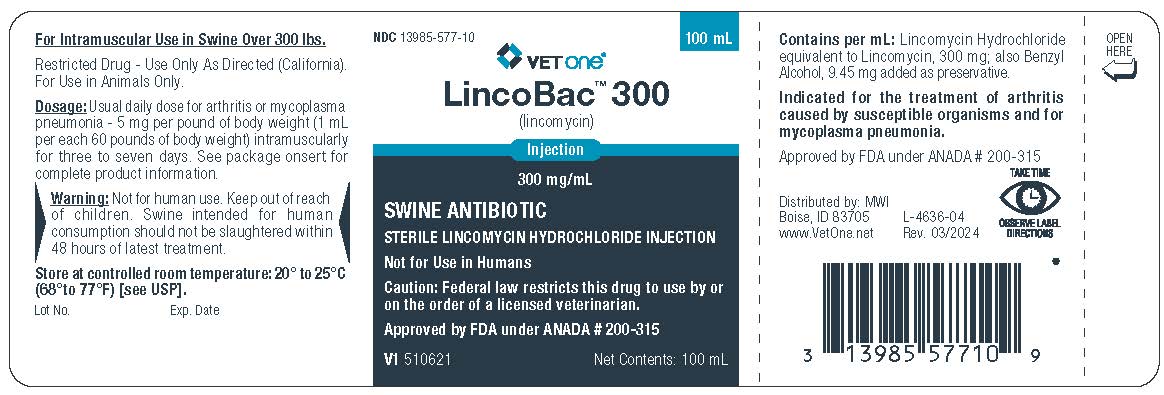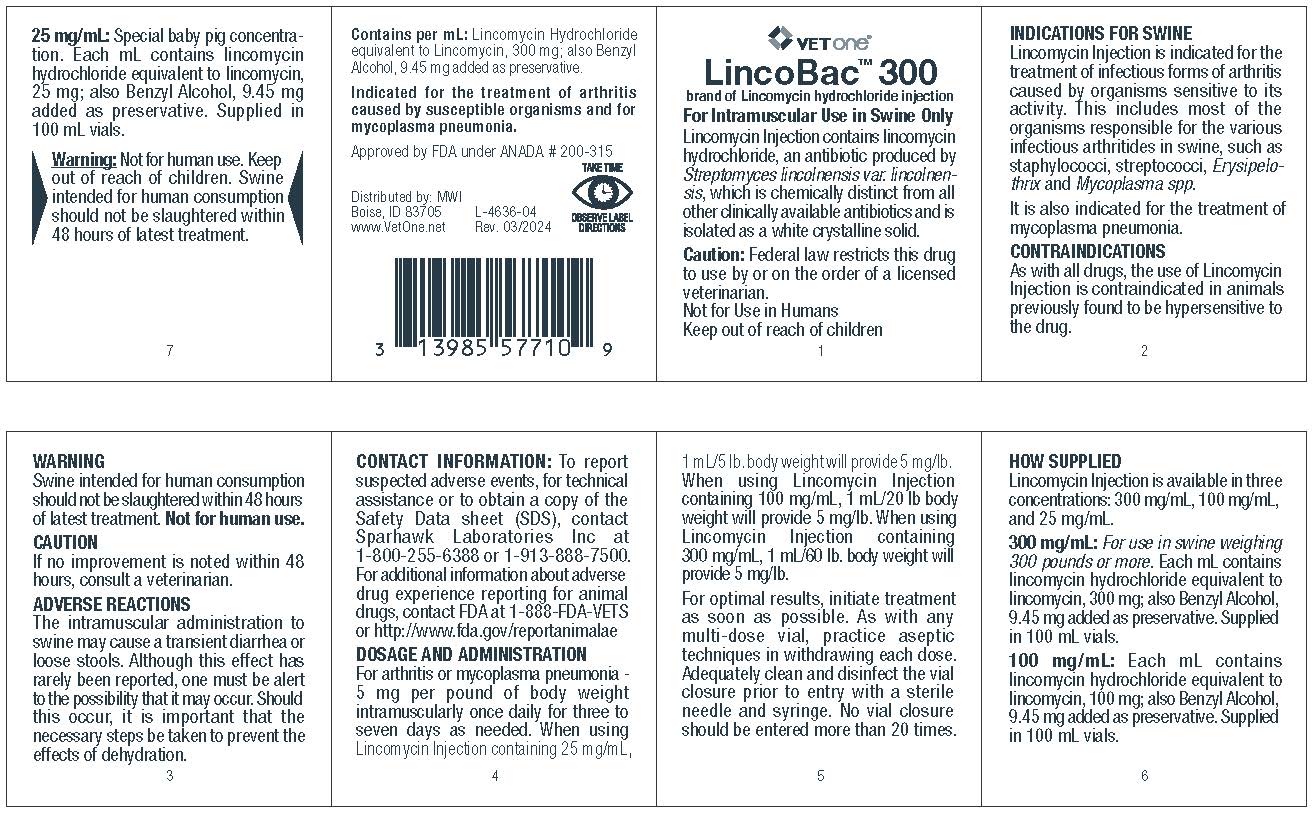 DRUG LABEL: LINCOMYCIN
NDC: 13985-577 | Form: INJECTION
Manufacturer: MWI Veterinary Supply, Inc.
Category: animal | Type: PRESCRIPTION ANIMAL DRUG LABEL
Date: 20240530

ACTIVE INGREDIENTS: LINCOMYCIN HYDROCHLORIDE 300 mg/1 mL
INACTIVE INGREDIENTS: BENZYL ALCOHOL 9.45 mg/1 mL

Linco-Bac 300

DESCRIPTION

(lincomycin)

brand of Lincomycin hydrochloride injectable

300 mg/mL

SWINE ANTIBIOTIC

STERILE LINCOMYCIN HYDROCHLORIDE INJECTION

Not for Use in Humans

Caution:Federal law restricts this drug to use by or on the order of a licensed veterinarian.

Approved by FDA under ANADA # 200-315

For Intramuscular Use in Swine Over 300 lbs.

Restricted Drug - Use Only As Directed (California).
For Use in Animals Only.

Lincomycin Injectable contains lincomycin hydrochloride, an antibiotic produced by Streptomyces lincolnensis var. lincolnensis, which is chemically distinct from all other clinically available antibiotics and is isolated as a white crystalline solid.

INDICATIONS FOR SWINE

Indicated for the treatment of arthritis caused by susceptible organisms and for mycoplasma pneumonia.

Lincomycin Injectable is indicated for the treatment of infectious forms of arthritis caused by organisms sensitive to its activity. This includes most of the organisms responsible for the various infectious arthritides in swine, such as staphylococci, streptococci, Erysipelothrix and Mycoplasma spp.

It is also indicated for the treatment of mycoplasma pneumonia.

CONTRAINDICATIONS

As with all drugs, the use of Lincomycin Injectable is contraindicated in animals previously found to be hypersensitive to the drug.

WARNING

Swine intended for human consumption should not be slaughtered within 48 hours of latest treatment. Not for human use.

CAUTION

If no improvement is noted within 48 hours, consult a veterinarian.

ADVERSE REACTIONS

The intramuscular administration to swine may cause a transient diarrhea or loose stools. Although this effect has rarely been reported, one must be alert to the possibility that it may occur. Should this occur, it is important that the necessary steps be taken to prevent the effects of dehydration.

DOSAGE AND ADMINISTRATION

Dosage:

Usual daily dose for arthritis or mycoplasma pneumonia - 5 mg per pound of body weight (1 mL per each 60 pounds of body weight) intramuscularly for three to seven days.

See package insert for complete product information:

For arthritis or mycoplasma pneumonia-5 mg per pound of body weight intramuscularly once daily for three to seven days as needed. When using Lincomycin Injectable containing 25 mg/mL, 1 mL/5 lb. body weight will provide 5 mg/lb. When using Lincomycin Injectable containing 100 mg/mL, 1 mL/20 lb body weight will provide 5 mg/lb. When using Lincomycin Injectable containing 300 mg/mL, 1 mL/60 lb. body weight will provide 5 mg/lb.

For optimal results, initiate treatment as soon as possible. As with any multi-dose vial, practice aseptic techniques in withdrawing each dose. Adequately clean and disinfect the vial closure prior to entry with a sterile needle and syringe. No vial closure should be entered more than 20 times.

HOW SUPPLIED

Lincomycin Injectable is available in three concentrations: 300 mg/mL, 100 mg/mL and 25 mg/mL.

300 mg/mL: For use in swine weighing 300 pounds or more. Each mL contains lincomycin hydrochloride equivalent to lincomycin, 300 mg; also Benzyl Alcohol, 9.45 mg added as preservative. Supplied in 100 mL vials.

100 mg/mL: Each mL contains lincomycin hydrochloride equivalent to lincomycin, 100 mg; also Benzyl Alcohol, 9.45 mg added as preservative. Supplied in 100 mL vials.

25 mg/mL: Special baby pig concentration. Each mL contains lincomycin hydrochloride equivalent to lincomycin, 25 mg; also Benzyl Alcohol, 9.45 mg added as preservative. Supplied in 100 mL vials.

COMPONENTS

Contains per mL: Lincomycin Hydrochloride equivalent to Lincomycin 300 mg; also Benzyl Alcohol, 9.45 mg added as preservative.

STORAGE AND HANDLING

Store at controlled room temperature: 20° to 25°C (68° to 77°F) [see USP]

TAKE TIME OBSERVE LABEL DIRECTIONS

Warning

Not for human use. Keep out of reach of children. Swine intended for human consumption should not be slaughtered within 48 hours in latest treatment.

CONTACT INFORMATION

To report suspected adverse events, for technical assistance or to obtain a copy of the Safety Data sheet (SDS), contact Sparhawk Laboratories Inc at 1-800-255-6388 or 1-913-888-7500. For additional information about adverse drug experience reporting for animal drugs, contact FDA at 1-888-FDA-VETS or http://www.fda.gov/reportanimalae